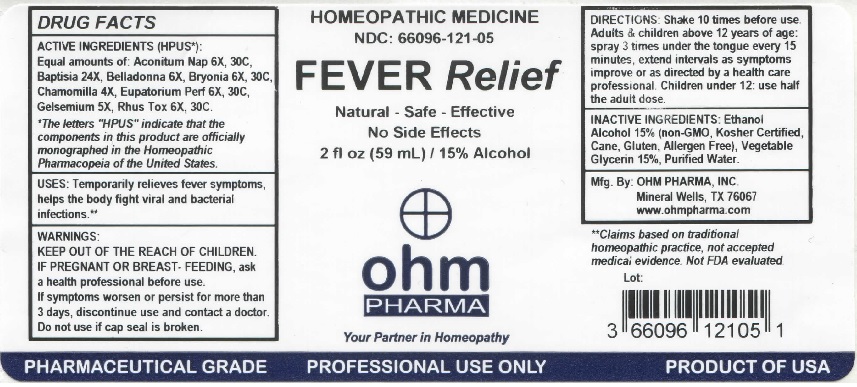 DRUG LABEL: OHM Fever Relief
NDC: 66096-121 | Form: SPRAY
Manufacturer: OHM PHARMA INC.
Category: homeopathic | Type: HUMAN OTC DRUG LABEL
Date: 20211229

ACTIVE INGREDIENTS: ACONITUM NAPELLUS 6 [hp_X]/59 mL; BAPTISIA TINCTORIA ROOT 24 [hp_X]/59 mL; ATROPA BELLADONNA 6 [hp_X]/59 mL; BRYONIA ALBA ROOT 6 [hp_X]/59 mL; MATRICARIA CHAMOMILLA 4 [hp_X]/59 mL; EUPATORIUM PERFOLIATUM FLOWERING TOP 6 [hp_X]/59 mL; GELSEMIUM SEMPERVIRENS ROOT 5 [hp_X]/59 mL; TOXICODENDRON PUBESCENS LEAF 6 [hp_X]/59 mL
INACTIVE INGREDIENTS: ALCOHOL; GLYCERIN; WATER

OHM Fever Relief

ACTIVE INGREDIENT

ACTIVE INGREDIENTS (HPUS*): Equal amounts of : Aconitum Nap 6X, 30C, Baptisia 24X, Belladonna 6X, Bryonia 6X, 30C, Chamomilla 4X, Eupatorium Perf 6X, 30C, Gelsemium 5X, Rhus Tox 6X, 30C.

*The letters "HPUS" indicate that the components in this product are officially monographed in the Homeopathic Pharmacopeia of the United States.

INDICATIONS AND USAGE

USES: Temporarily relieves fever symptoms, helps the body fight viral and bacterial infections.**

**Claims based on traditional homeopathic practice, not accepted medical evidence. Not FDA evaluated.

WARNINGS

WARNINGS: IF PREGNANT OR BREAST-FEEDING, ask a health professional before use. If symptoms worsen or persist for more than 3 days, discontinue use and contact a doctor.

- KEEP OUT OF REACH OF CHILDREN.

DOSAGE AND ADMINISTRATION

DIRECTIONS: Shake 10 times before use. Adults & children above 12 years of age: spray 3 times under the tongue every 15 minutes, extend intervals as symptoms improve or as directed by a health care professional. Children under 12 years: use half the adult dose.

Do not use if cap seal is broken.

INACTIVE INGREDIENT

INACTIVE INGREDIENTS: Ethanol Alcohol 15% (non-GMO, Kosher Certified, Cane, Gluten, Allergen Free), Vegetable Glycerin 15%, Purified Water.

QUESTIONS

Mfg. By: OHM PHARMA, INC. Mineral Wells, TX 76067

www.ohmpharma.com

PACKAGE LABEL

HOMEOPATHIC MEDICINE

NDC: 66096-121-05

FEVER Relief

Natural - Safe - Effective

No Side Effects

2 fl oz (59 mL) / 15% Alcohol

PURPOSE

Fever